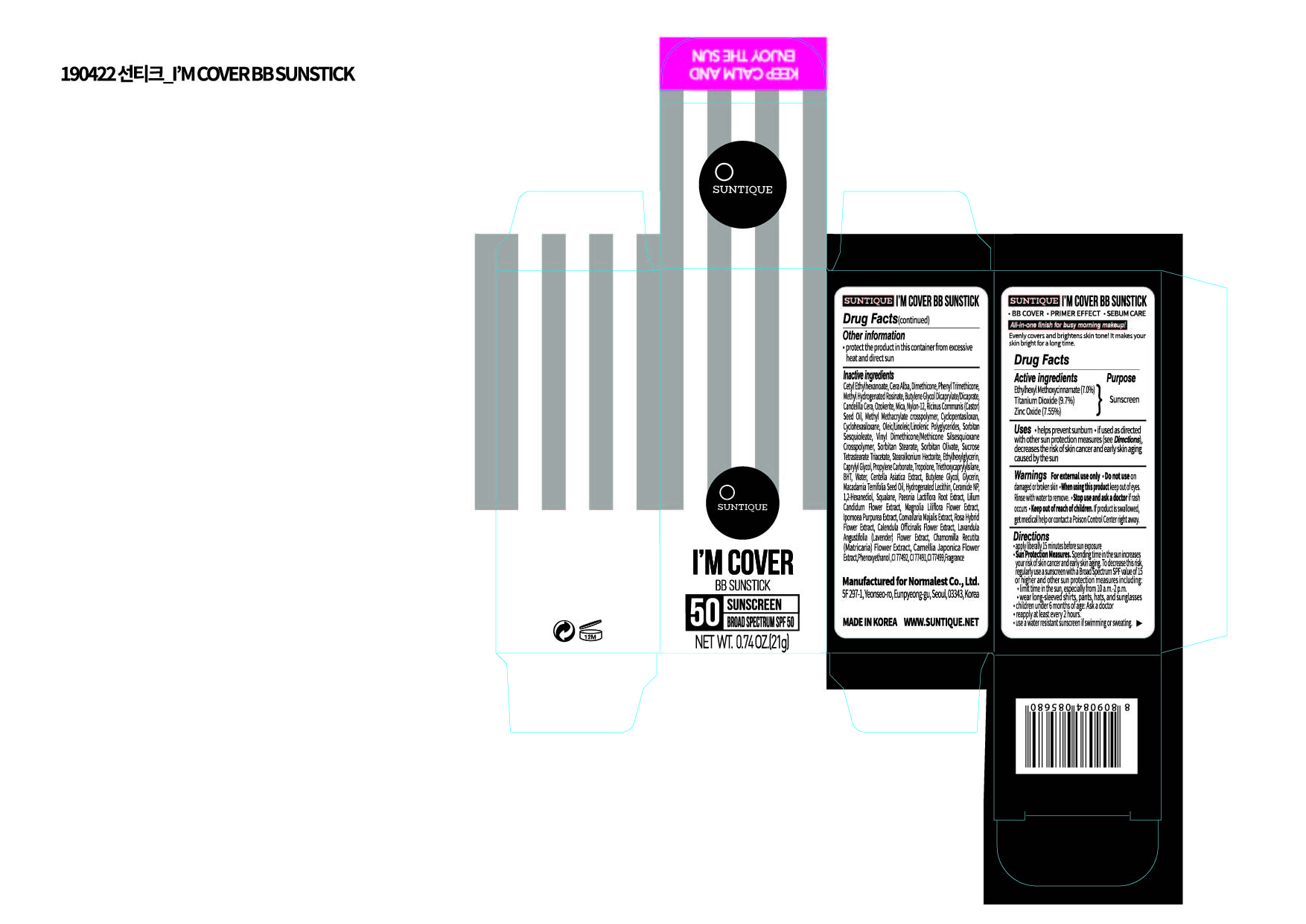 DRUG LABEL: IM COVER BB SUNSTICK
NDC: 72284-0003 | Form: STICK
Manufacturer: Normalest Co., Ltd.
Category: otc | Type: HUMAN OTC DRUG LABEL
Date: 20190422

ACTIVE INGREDIENTS: TITANIUM DIOXIDE 2.037 g/21 g; ZINC OXIDE 1.585 g/21 g; OCTINOXATE 1.47 g/21 g
INACTIVE INGREDIENTS: CONVALLARIA MAJALIS; CAMELLIA JAPONICA FLOWER; 1,2-HEXANEDIOL; NYLON-12; SORBITAN SESQUIOLEATE; SUCROSE TETRASTEARATE TRIACETATE; STEARALKONIUM HECTORITE; ETHYLHEXYLGLYCERIN; PROPYLENE CARBONATE; TROPOLONE; CETYL ETHYLHEXANOATE; DIMETHICONE; PHENYL TRIMETHICONE; METHYL HYDROGENATED ROSINATE; CENTELLA ASIATICA; SQUALANE; IPOMOEA PURPUREA TOP; LAVANDULA ANGUSTIFOLIA FLOWER; PHENOXYETHANOL; FERRIC OXIDE YELLOW; BUTYLATED HYDROXYTOLUENE; SORBITAN OLIVATE; CAPRYLYL GLYCOL; TRIETHOXYCAPRYLYLSILANE; WATER; MICA; RICINUS COMMUNIS SEED; METHYL METHACRYLATE/GLYCOL DIMETHACRYLATE CROSSPOLYMER; WHITE WAX; BUTYLENE GLYCOL DICAPRYLATE/DICAPRATE; CANDELILLA WAX; SORBITAN MONOSTEARATE; GLYCERIN; MACADAMIA OIL; HYDROGENATED SOYBEAN LECITHIN; PAEONIA LACTIFLORA ROOT; LILIUM CANDIDUM FLOWER; MAGNOLIA LILIIFLORA FLOWER; CALENDULA OFFICINALIS FLOWER; CHAMOMILE; FERRIC OXIDE RED; FERROSOFERRIC OXIDE; BUTYLENE GLYCOL; CERAMIDE NP

PACKAGE LABEL

Active Ingredients

Titanium Dioxide, Zinc Oxide, Ethylhexyl Methoxycinnamate

Inactive Ingredients

Cetyl Ethylhexanoate, Cera Alba, Dimethicone, Phenyl Trimethicone, Methyl Hydrogenated Rosinate , Butylene Glycol, Dicaprylate/Dicaprate, Candelilla Cera, Ozokerite, Mica, Nylon-12, Ricinus Communis (Castor) Seed Oil, Methyl Methacrylate crosspolymer, Cyclopentasiloxan, Cyclohexasiloxane, Oleic/Linoleic/Linolenic Polyglycerides, Sorbitan Sesquioleate, Vinyl Dimethicone/Methicone Silsesquioxane Crosspolymer, Sorbitan Stearate, Sorbitan Olivate, Sucrose Tetrastearate Triacetate , Stearalkonium Hectorite, Ethylhexylglycerin, Caprylyl Glycol, Propylene Carbonate, Tropolone, Triethoxycaprylylsilane, BHT , AQUA, Centella Asiatica Extract, Butylene Glycol, Glycerin, Macadamia Ternifolia Seed Oil, Hydrogenated Lecithin, Ceramide NP, 1,2-Hexanediol, Squalane, Paeonia Lactiflora Root Extract, Lilium Candidum Flower Extract, Magnolia Liliflora Flower Extract, Ipomoea Purpurea Extract, Convallaria Majalis Extract, Rosa Hybrid Flower Extract, Calendula Officinalis Flower Extract, Lavandula Angustifolia Flower Extract, Chamomilla Recutita Flower Extract , Camellia Japonica Flower Extract, Phenoxyethanol , CI 77492, CI 77491, CI 77499, Fragrance